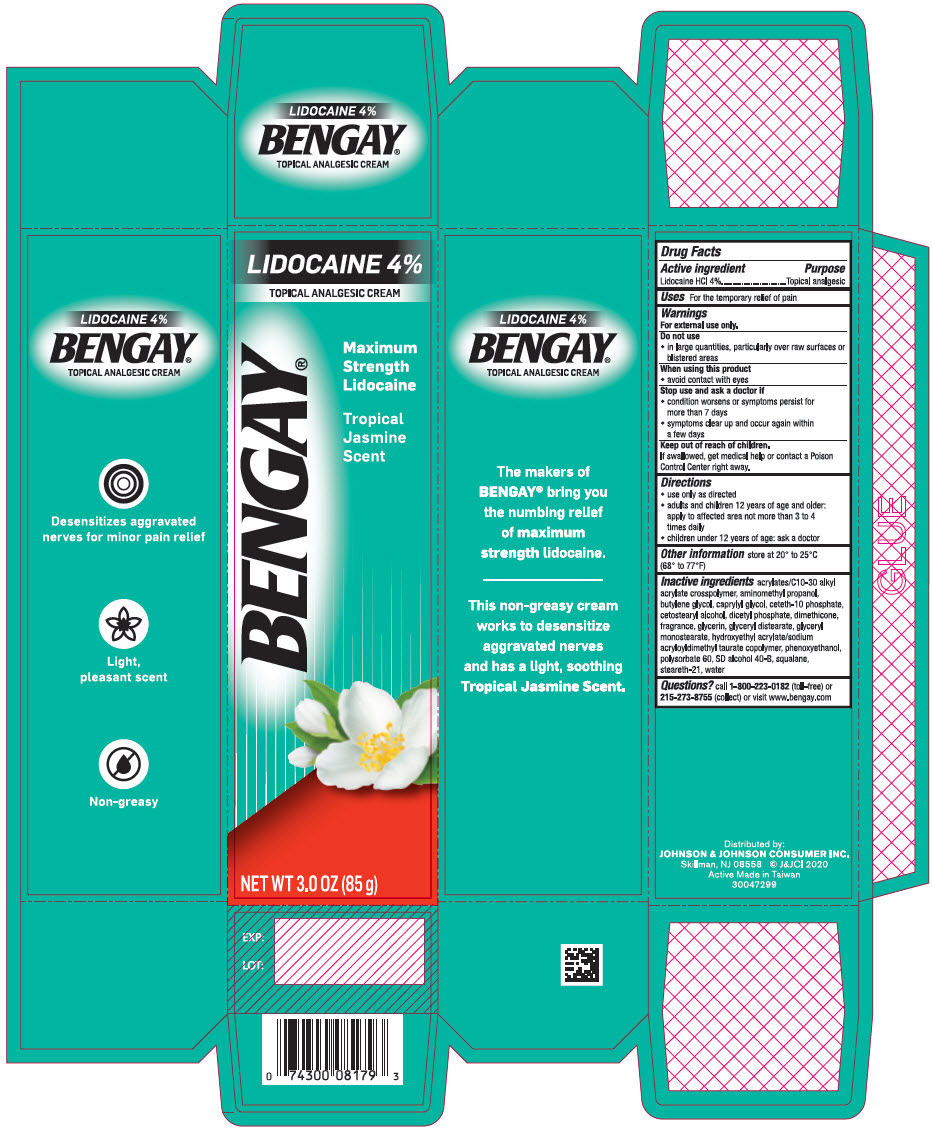 DRUG LABEL: BENGAY
NDC: 69968-0614 | Form: CREAM
Manufacturer: Kenvue Brands LLC
Category: otc | Type: HUMAN OTC DRUG LABEL
Date: 20241106

ACTIVE INGREDIENTS: LIDOCAINE 40 mg/1 g
INACTIVE INGREDIENTS: CARBOMER INTERPOLYMER TYPE A (ALLYL SUCROSE CROSSLINKED); AMINOMETHYLPROPANOL; BUTYLENE GLYCOL; CAPRYLYL GLYCOL; CETETH-10 PHOSPHATE; CETOSTEARYL ALCOHOL; DIHEXADECYL PHOSPHATE; DIMETHICONE; GLYCERIN; GLYCERYL DISTEARATE; GLYCERYL MONOSTEARATE; HYDROXYETHYL ACRYLATE/SODIUM ACRYLOYLDIMETHYL TAURATE COPOLYMER (100000 MPA.S AT 1.5%); PHENOXYETHANOL; POLYSORBATE 60; ALCOHOL; SQUALANE; STEARETH-21; WATER

BENGAY® TROPICAL JASMINE

Drug Facts

Active ingredient

Lidocaine HCl 4%

Purpose

Topical analgesic

Uses

For the temporary relief of pain

Warnings

For external use only.

Do not use

- in large quantities, particularly over raw surfaces or blistered areas

When using this product

- avoid contact with eyes

Stop use and ask a doctor if

- condition worsens or symptoms persist for more than 7 days
- symptoms clear up and occur again within a few days

Keep out of reach of children. If swallowed, get medical help or contact a Poison Control Center right away.

Directions

- use only as directed
- adults and children 12 years of age and older: apply to affected area not more than 3 to 4 times daily
- children under 12 years of age: ask a doctor

Other information

store at 20° to 25°C (68° to 77°F)

Inactive ingredients

acrylates/C10-30 alkyl acrylate crosspolymer, aminomethyl propanol, butylene glycol, caprylyl glycol, ceteth-10 phosphate, cetostearyl alcohol, dicetyl phosphate, dimethicone, fragrance, glycerin, glyceryl distearate, glyceryl monostearate, hydroxyethyl acrylate/sodium acryloyldimethyl taurate copolymer, phenoxyethanol, polysorbate 60, SD alcohol 40-B, squalane, steareth-21, water

Questions?

call 1-800-223-0182 (toll-free) or 215-273-8755 (collect) or visit www.bengay.com

Distributed by:
JOHNSON & JOHNSON CONSUMER INC.
Skillman, NJ 08558

PRINCIPAL DISPLAY PANEL - 85 g Tube Carton

LIDOCAINE 4%
TOPICAL ANALGESIC CREAM
BENGAY®
Maximum
Strength
Lidocaine

Tropical
Jasmine
Scent

NET WT 3.0 OZ (85 g)